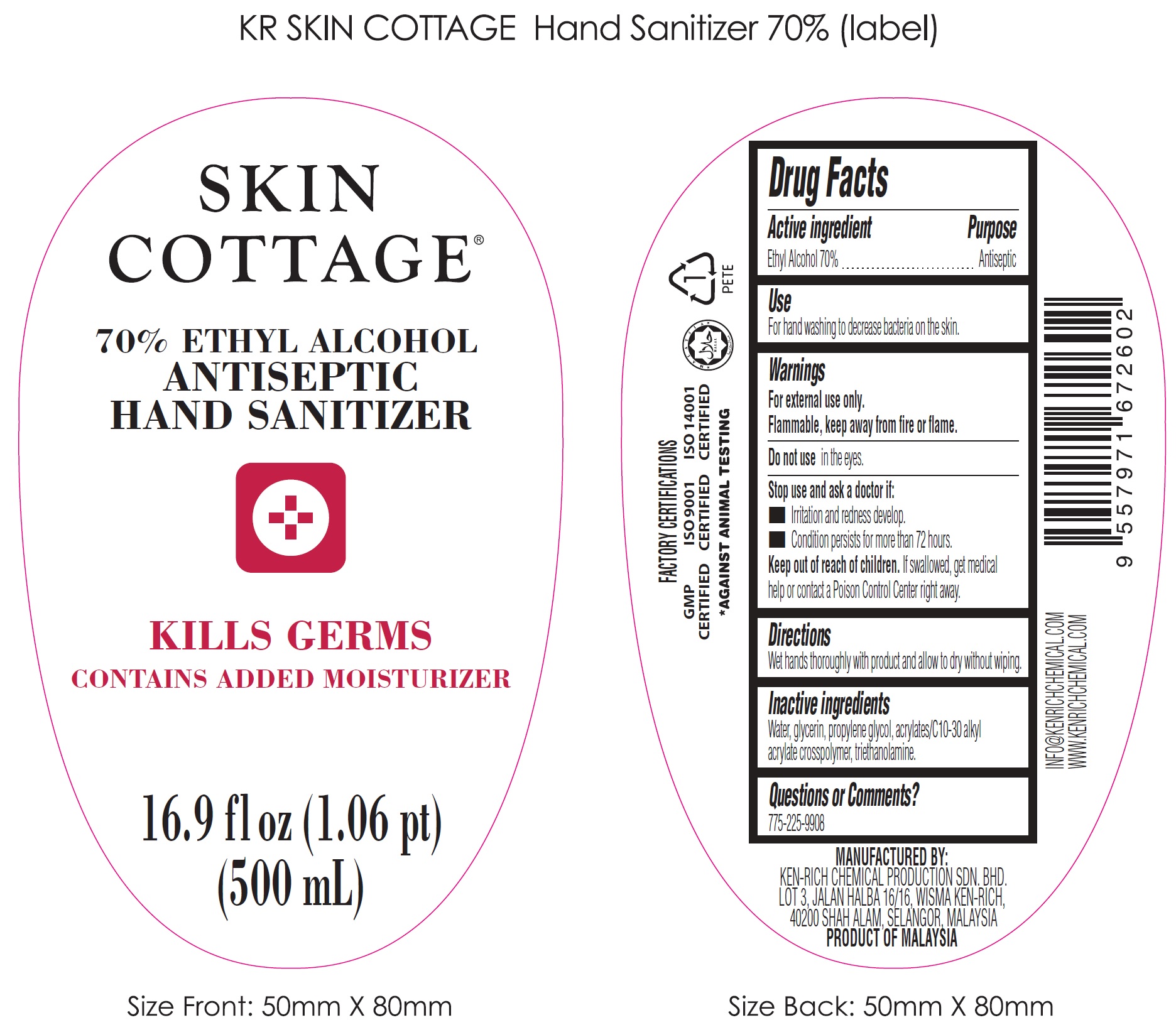 DRUG LABEL: Skin Cottage 70 Percent Ethyl Alcohol Antiseptic Hand Sanitizer
NDC: 79468-001 | Form: GEL
Manufacturer: KEN-RICH CORPORATION SDN. BHD.
Category: otc | Type: HUMAN OTC DRUG LABEL
Date: 20240711

ACTIVE INGREDIENTS: ALCOHOL 0.7 mL/1 mL
INACTIVE INGREDIENTS: WATER; GLYCERIN; PROPYLENE GLYCOL; CARBOMER INTERPOLYMER TYPE A (ALLYL SUCROSE CROSSLINKED); TROLAMINE

Skin Cottage 70% Ethyl Alcohol Antiseptic Hand Sanitizer

Active ingredient

Ethyl Alcohol 70%

Purpose

Antiseptic

Use

For hand washing to decrease bacteria on the skin.

Warnings

For external use only. Flammable, keep away from fire or flame.

Do not use

in the eyes.

Stop use and ask a doctor if:

- Irritation and redness develop.
- Condition persists for more than 72 hours.

Keep out of reach of children.

If swallowed, get medical help or contact a Poison Control Center right away.

Directions

Wet hands thoroughly with product and allow to dry without wiping.

Inactive ingredients

Water, glycerin, propylene glycol, acrylates/C10-30 alkyl acrylate crosspolymer, triethanolamine.

Questions or Comments?

775-225-9908